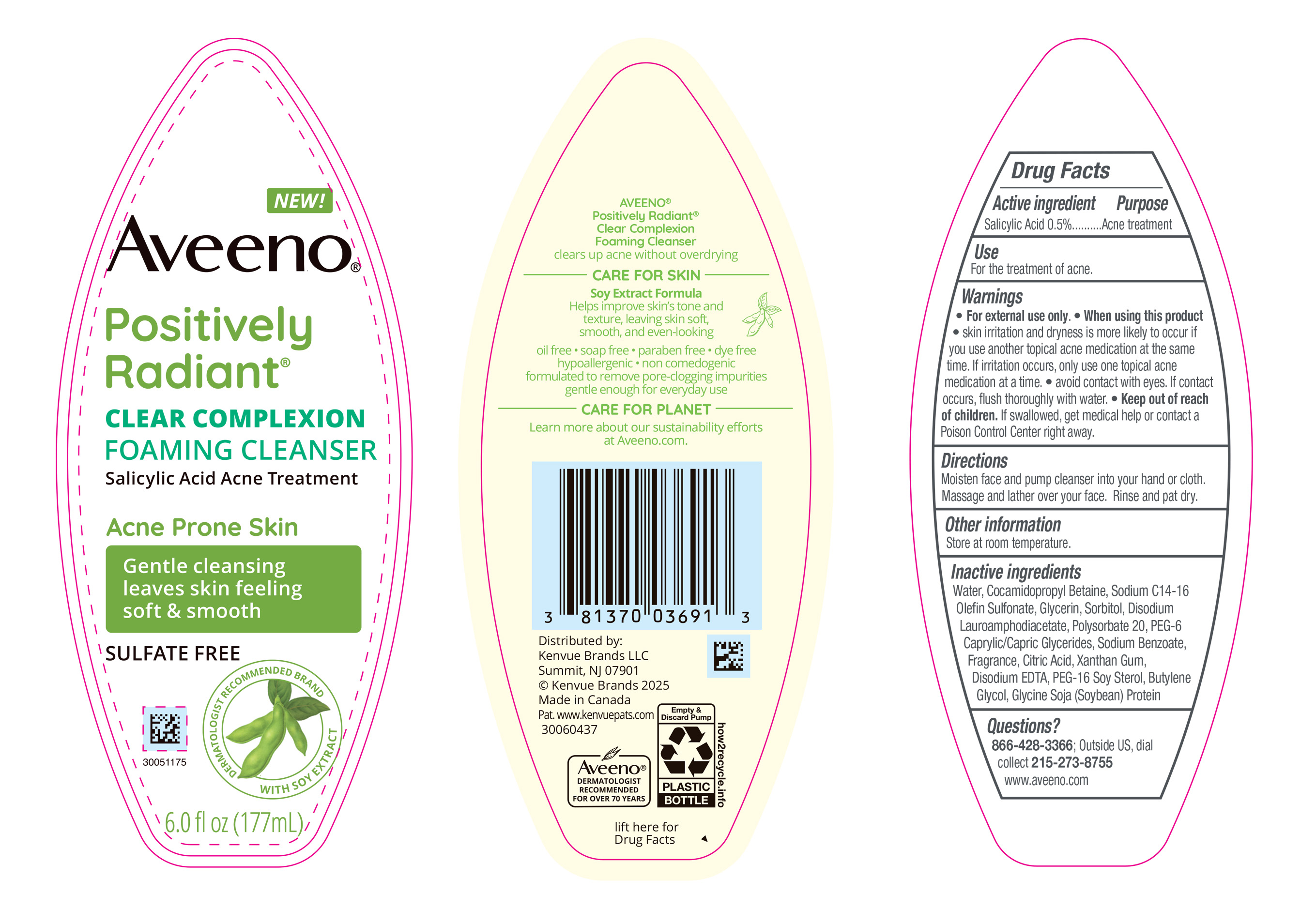 DRUG LABEL: Aveeno Positively Radiant Clear Complexion Foaming Cleanser
NDC: 69968-0769 | Form: LIQUID
Manufacturer: Kenvue Brands LLC
Category: otc | Type: HUMAN OTC DRUG LABEL
Date: 20250526

ACTIVE INGREDIENTS: SALICYLIC ACID 5 mg/1 mL
INACTIVE INGREDIENTS: DISODIUM LAUROAMPHODIACETATE; POLYSORBATE 20; WATER; COCAMIDOPROPYL BETAINE; SODIUM C14-16 OLEFIN SULFONATE; SODIUM BENZOATE; PEG-6 CAPRYLIC/CAPRIC GLYCERIDES; XANTHAN GUM; SOY PROTEIN; BUTYLENE GLYCOL; CITRIC ACID MONOHYDRATE; EDETATE DISODIUM ANHYDROUS; PEG-16 SOY STEROL; GLYCERIN; SORBITOL

Aveeno Positively Radiant Clear Complexion Foaming Cleanser

Drug Facts

Active ingredient

Active Ingredient Purpose

Salicylic Acid 0.5%

Purpose

Acne treatment

Use

For the treatment of acne.

Warnings

For external use only.

When using this product

• skin irritation and dryness is more likely to occur if you use another topical acne medication at the same time. If irritation occurs, only use one topical acne medication at a time.

• avoid contact with eyes. If contact occurs, flush thoroughly with water

• Keep out of reach of children. If swallowed, get medical help or contact a Poison Control Center right away.

Directions

- Moisten face and pump cleanser into your hand or cloth. Massage and lather over your face. Rinse and pat dry.

Other information

Store at room temperature.

Inactive ingredients

Water, Cocamidopropyl Betaine, Sodium C14-16 Olefin Sulfonate, Glycerin, Sorbitol, Disodium Lauroamphodiacetate, Polysorbate 20, PEG-6 Caprylic/Capric Glycerides, Sodium Benzoate, Fragrance, Citric Acid, Xanthan Gum, Disodium EDTA, PEG-16 Soy Sterol, Butylene Glycol, Glycine Soja (Soybean) Protein

Questions?

866-428-3366; Outside US, dial collect 215-273-8755 www.aveeno.com

Distributed by:
Kenvue Brands LLC
Summit, NJ 07901

PRINCIPAL DISPLAY PANEL - BOTTLE, PUMP 177 mL

NEW!

Aveeno®

Positively

Radiant®

CLEAR COMPLEXION

FOAMING CLEANSER

Salicylic Acid Acne Treatment

Acne Prone Skin

Gentle cleansing

leaves skin feeling

soft & smooth

SULFATE FREE

DERMATOLOGIST RECOMMENDED BRAND

WITH SOY EXTRACT

6.0 fl oz (177mL)